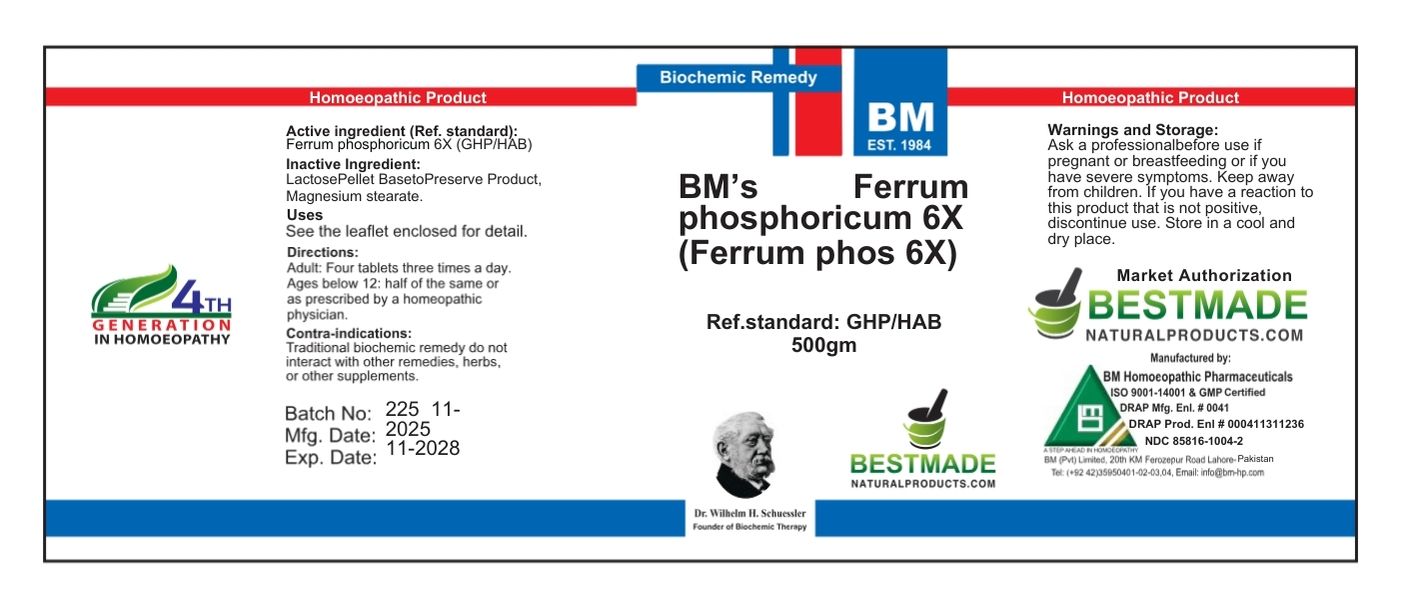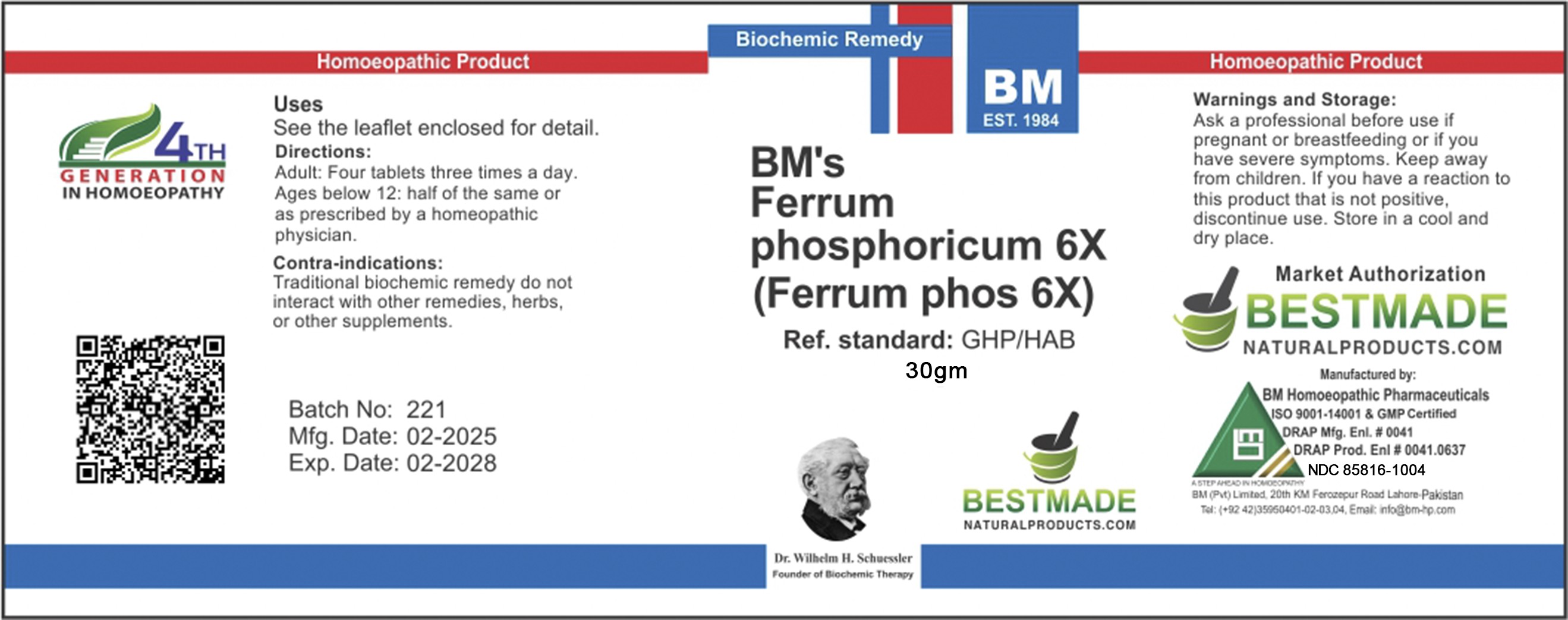 DRUG LABEL: BM Ferr Phos
NDC: 85816-1004 | Form: TABLET
Manufacturer: BM Private Limited
Category: homeopathic | Type: HUMAN OTC DRUG LABEL
Date: 20251202

ACTIVE INGREDIENTS: FERROSOFERRIC PHOSPHATE 6 [hp_X]/60 mg
INACTIVE INGREDIENTS: MAGNESIUM STEARATE 1.25 mg/60 mg; LACTOSE 58.6 mg/60 mg

BM ferr phos 6x

CONTRAINDICATIONS

Contra-indications:
Traditional biochemic remedy do not interact with other remedies, herbs, or other supplements.

Directions:
Adult: Four tablets three times a day.
Ages below 12: half of the same or as prescribed by a homeopathic physician.

Inactive ingredients: Lactose; MAGNESIUM STEARATE

ACTIVE INGREDIENT

Ferrum Phosphoricum

Warnings and Storage:

Ask a professional before use if pregnant or breastfeeding or if you have severe symptoms. Keep away from children. If you have a reaction to this product that is not positive, discontinue use. Store in a cool and dry place.

KEEP OUT OF REACH OF CHILDREN

Warnings and Storage:

Ask a professional before use if pregnant or breastfeeding or if you have severe symptoms. Keep away from children. If you have a reaction to this product that is not positive, discontinue use. Store in a cool and dry place.

Uses
See the leaflet enclosed for detail

Uses
See the leaflet enclosed for detail.

package 1 (30g)

package 2 (500g)